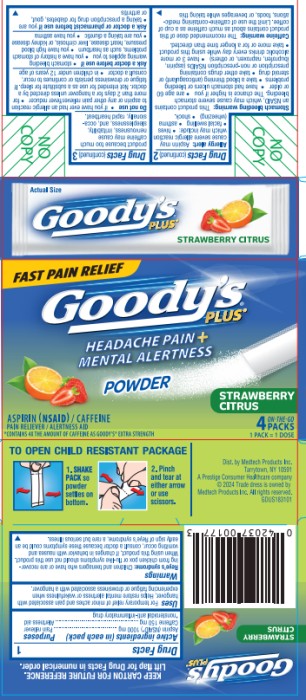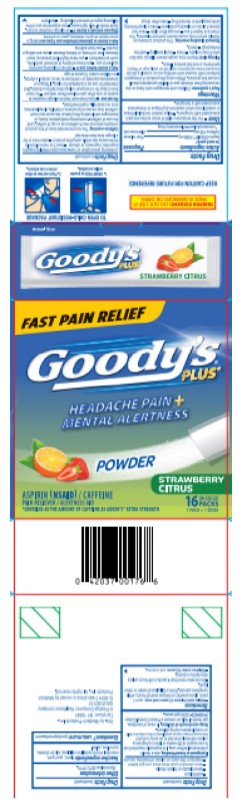 DRUG LABEL: GOODYS Mental Alert
NDC: 63029-667 | Form: POWDER
Manufacturer: Medtech Products Inc.
Category: otc | Type: HUMAN OTC DRUG LABEL
Date: 20250217

ACTIVE INGREDIENTS: ASPIRIN 1000 mg/1 1; CAFFEINE 150 mg/1 1
INACTIVE INGREDIENTS: GUAR GUM; MANNITOL; MICROCRYSTALLINE CELLULOSE; SILICON DIOXIDE; SUCRALOSE; XYLITOL

Goodys Mental Alert

Drug Facts

Active ingredients

(in each pack):

Purposes

Aspirin (NSAID*) 1000 mg…………………………………......Pain reliever

Caffeine 150 mg……………………………….…………………Alertness aid

*nonsteroidal anti-inflammatory drug

Uses

- For the temporary relief of minor aches and pains associated with hangover.
- Helps restore mental alertness or wakefulness when experiencing fatigue or drowsiness associated with a hangover.

Warnings:

Reye’s syndrome: Children and teenagers who have or are recovering from chicken pox or flu-like symptoms should not use this product. When using this product, if changes in behavior with nausea and vomiting occur, consult a doctor because these symptoms could be an early sign of Reye’s syndrome, a rare but serious illness.

Allergy alert: Aspirin may cause severe allergic reaction which may include:

- hives
- facial swelling
- asthma (wheezing)
- shock.

Stomach bleeding warning: This product contains an NSAID, which may cause severe stomach bleeding. The chance is higher if you

- are age 60 or older
- have had stomach ulcers or bleeding problems
- take a blood thinning (anticoagulant) or steroid drug
- take other drugs containing prescription or non-prescription NSAIDs (aspirin, ibuprofen, naproxen, or others)
- have 3 or more alcoholic drinks every day while using this product
- take more or for a longer time than directed.

Caffeine warning:

The recommended dose of this product contains about as much caffeine as a cup of coffee. Limit the use of caffeine-containing medications, foods, or beverages while taking this product because too much caffeine may cause nervousness, irritability, sleeplessness, and, occasionally, rapid heartbeat.

Do not use

- if you have ever had an allergic reaction to aspirin or any other pain reliever/fever reducer
- for more than 2 days for a hangover unless directed by a doctor. Not intended for use as a substitute for sleep. If fatigue or drowsiness persists or continues to recur, consult a doctor.
- in children under 12 years of age

Ask a doctor before use if

- stomach bleeding warning applies to you
- you have a history of stomach problems, such as heartburn
- you have high blood pressure, heart disease, liver cirrhosis, or kidney disease
- you are taking a diuretic
- you have asthma

Ask a doctor or pharmacist before use if you are

- taking a prescription drug for diabetes, gout, or arthritis

Stop use and ask a doctor if

- an allergic reaction occurs. Seek medical help right away
- you experience any of the following signs of stomach bleeding:
  - feel faint
  - vomit blood
  - have bloody or black stools
  - have stomach pain that does not get better
  - ringing in the ears or a loss of hearing occurs

If pregnant or breast-feeding,

ask a health professional before use. It is especially important not to use aspirin at 20 weeks or later in pregnancy unless definitely directed to do so by a doctor because it may cause problems in the unborn child or complications during delivery.

Keep out of reach of children.

In case of overdose, get medical help or contact a Poison Control Center (1-800-222-1222) right away.

Directions:

- Adults and children 12 years and over: open 1 pack, place powder on tongue every 6 hours, while symptoms persist. Drink a full glass of water or other liquid.
- Do not take more than 4 packs in 24 hours unless directed by a doctor.
- Children under 12 years: ask a doctor.

Other information

Store below 25°C (77°F)

Inactive ingredients

flavor, guar gum, mannitol, microcrystalline cellulose, silicon dioxide, sucralose, xylitol.

Questions?

1-866-255-5197 goodyspowder.com

Dist. by Medtech Products Inc.
Tarrytown, NY 10591
A Prestige Consumer Healthcare company

© 2024 Trade dress is owned by Medtech Products Inc. All rights reserved.

PRINCIPAL DISPLAY PANEL

Goody’s Mental Alert
Aspirin (NSAID)

Caffeine
Pain Reliever
Alertness Aid
4 POWDERS

PRINCIPAL DISPLAY PANEL

Goody’s Mental Alert
Aspirin (NSAID)

Caffeine
Pain Reliever
Alertness Aid
16 POWDERS